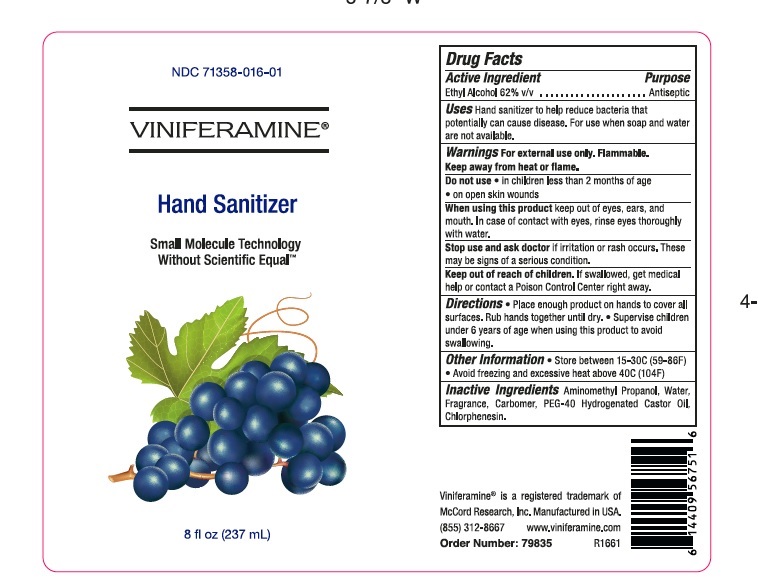 DRUG LABEL: VINIFERAMINE HAND SANITIZER
NDC: 71358-016 | Form: GEL
Manufacturer: MCCORD RESEARCH
Category: otc | Type: HUMAN OTC DRUG LABEL
Date: 20220125

ACTIVE INGREDIENTS: ALCOHOL 620 mg/1 mL
INACTIVE INGREDIENTS: AMINOMETHYLPROPANOL; WATER; CARBOMER HOMOPOLYMER, UNSPECIFIED TYPE; POLYOXYL 40 HYDROGENATED CASTOR OIL; CHLORPHENESIN

VINIFERAMINE HAND SANITIZER GEL

Active lngredient

Ethyl Alcohol

Purpose

Antiseptic

Uses

Hand sanitizer to help reduce bacteria that potentially can cause disease. For use when soap and water are not available.

Warnings

For external use only. Flammable. Keep away from heat or flame
Do not use
• in children less than 2 months of age
• on open skin wounds
When using this product keep out of eyes, ears, and mouth. In case of contact with eyes, rinse eyes thoroughly with water.
Stop use and ask a doctor if irritation or rash occurs. These may be signs of a serious condition.
Keep out of reach of children. If swallowed, get medical help or contact a Poison Control Center right away.

Directions

Place enough product on hands to cover all surfaces. Rub hands together until dry. • Supervise children under 6 years of age when using this product to avoid swallowing

Inactives

Aminomethyl Propanol, Water, Fragrance, Carbomer, PEG-40 Hydrogenated Castor Oil, Chlorphenesin.